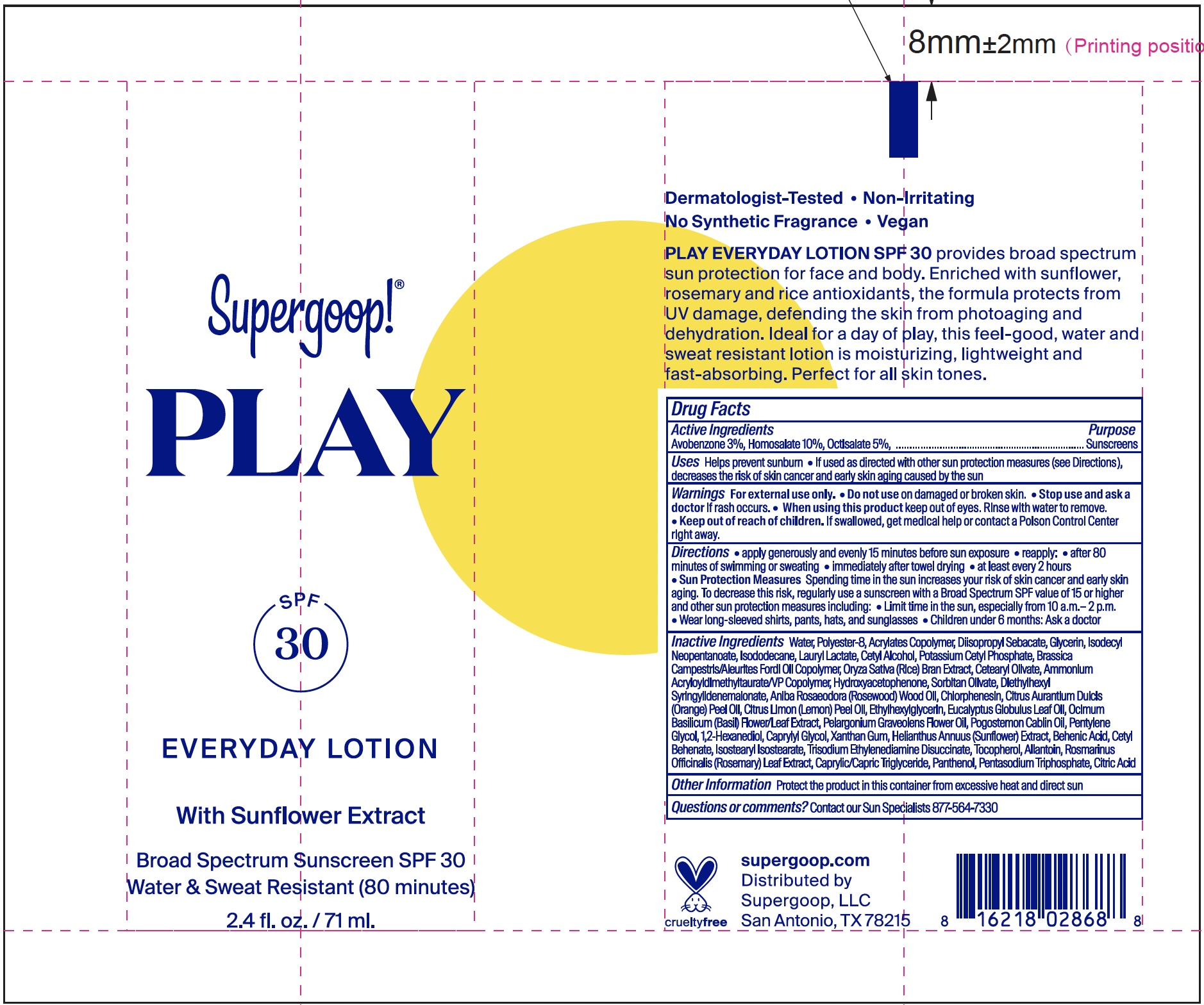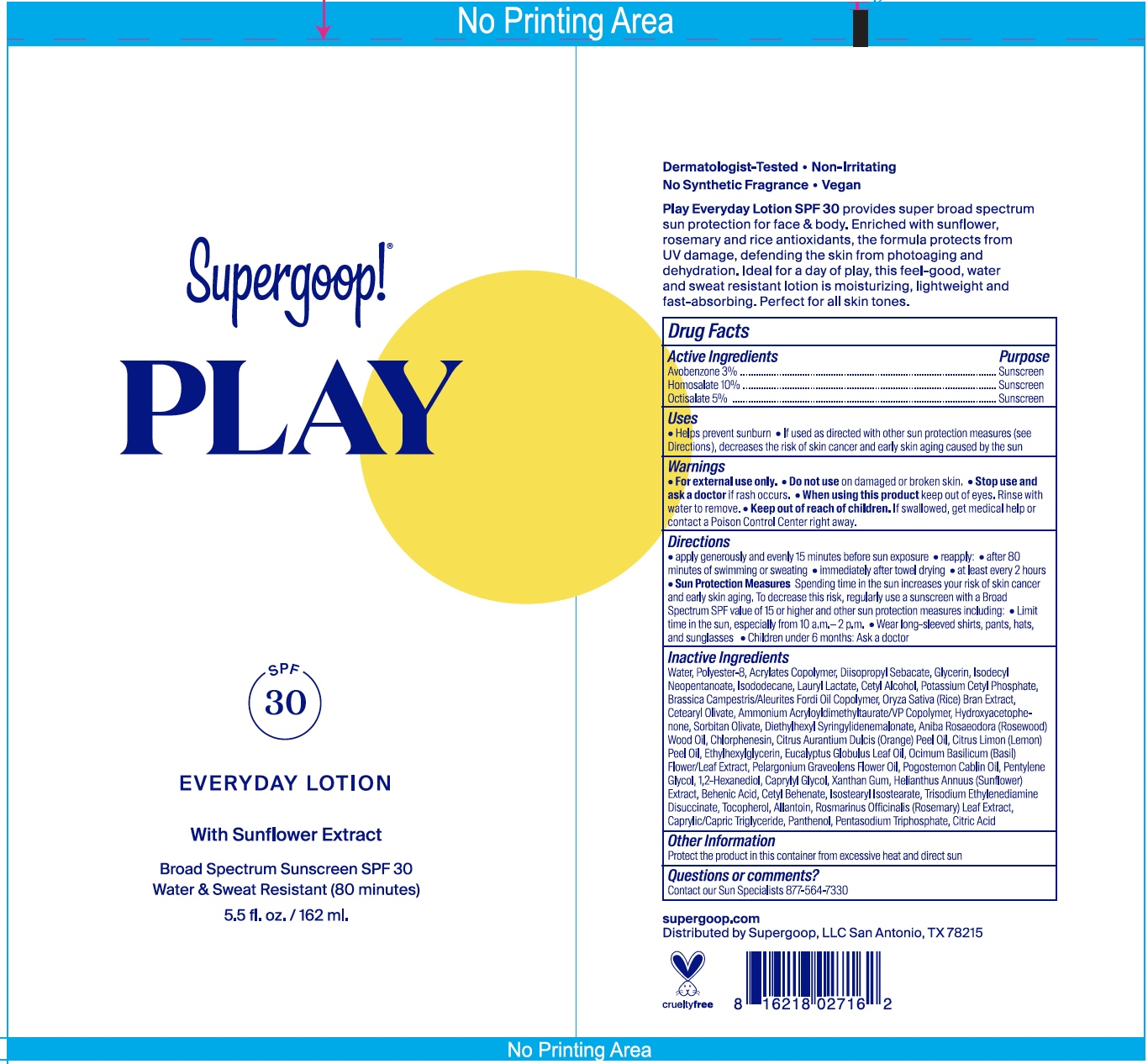 DRUG LABEL: Everyday Sunscreen with Sunflower Extract Broad Spectrum SPF 30
NDC: 75936-210 | Form: CREAM
Manufacturer: Supergoop, LLC
Category: otc | Type: HUMAN OTC DRUG LABEL
Date: 20240416

ACTIVE INGREDIENTS: AVOBENZONE 3 g/100 mL; HOMOSALATE 10 g/100 mL; OCTISALATE 5 g/100 mL
INACTIVE INGREDIENTS: POLYESTER-8 (1400 MW, CYANODIPHENYLPROPENOYL CAPPED); EUCALYPTUS GLOBULUS LEAF; CITRIC ACID MONOHYDRATE; DIETHYLHEXYL SYRINGYLIDENEMALONATE; ROSEWOOD OIL; CHLORPHENESIN; ORANGE OIL; LEMON OIL; GLYCERIN; ISODECYL NEOPENTANOATE; ETHYLHEXYLGLYCERIN; 1,2-HEXANEDIOL; CAPRYLYL GLYCOL; XANTHAN GUM; ALLANTOIN; PANTHENOL; SODIUM TRIPOLYPHOSPHATE ANHYDROUS; WATER; BUTYL ACRYLATE/METHYL METHACRYLATE/METHACRYLIC ACID COPOLYMER (18000 MW); DIISOPROPYL SEBACATE; ISODODECANE; LAURYL LACTATE; CETYL ALCOHOL; POTASSIUM CETYL PHOSPHATE; RICE BRAN; CETEARYL OLIVATE; HYDROXYACETOPHENONE; SORBITAN OLIVATE; PELARGONIUM GRAVEOLENS FLOWER OIL; PENTYLENE GLYCOL; TRISODIUM ETHYLENEDIAMINE DISUCCINATE; BEHENIC ACID; CETYL BEHENATE; ISOSTEARYL STEARATE; TOCOPHEROL; MEDIUM-CHAIN TRIGLYCERIDES

Everyday SPF 30 with Sunflower Extract

Active Ingredients Purpose

Avobenzone 3% Sunscreen

Homosalate 10% Sunscreen

Octisalate 5% Sunscreen

Uses

- Helps prevent sunburn
- If used as directed with other sun protection measures (see DIrections), decreases the risk of skin cancer and early skin aging casused by the sun

Keep out of reach of children. If product is swallowed, get medical help or contact a Poison Control Center right away.

Stop use and ask a doctor if rash occurs.

Warnings

For external use only

Do not use on damaged or broken skin.

When using this product keep out of eyes. Rinse with water to remove.

Directions

- Apply gerenously and evenly 15 minutes before sun exsposure
- Reapply

after 80 minutes of swimming or sweating

immediately after towel drying

at least every 2 hours

- Sun Protection Measures Spending time in the sun increases your risk of skin cancer and early skin aging. To decrease this risk, regularly use a sunscreen with a broad spectrum SPF value of 15 or higher and other sun protection measures including:
- Limit time in the sun, especially from 10 a.m.- 2 p.m.
- Wear long-sleeved shirts, pants, hats, and sunglasses
- Children under 6 months: Ask a doctor

Inactive Ingredients

Water, Polyester-8, Acrylates Copolymer, Diisopropyl Sebacate, Glycerin, Isodecyl Neopentanoate, Isododecane, Lauryl Lactate, Cetyl Alcohol, Potassium Cetyl Phosphate, Brassica Campstris/Aleurites Fordi Oil Copolymer, Oryza Sativa (Rice) Bran Extract, Cetearyl Olivate, Ammonium Acryloyldimethyltaurate/ VP Copolymer, Hydroxyacetophenone, Sorbitan Olivate, Diethylhexyl Syringylidenemalonate, Aniba Roseodora (Rosewood) Wood Oil, Chlorphenesin, Citrus Aurantium Dulcis (Orange) Peel Oil, Citrus Limon (Lemon) Peel Oil, Ethyhexylglycerin, Eucaluptyus Globulus Leaf Oil, Ocimum Basilicum (Basil) Flower/Leaf Extract, Pelargonium Graveolens Flower Oil, Pogostemon Cablin Oil, Pentylene Glycol, 1,2-Hexanediol, Caprylyl Glycol, Xanthan Gum, Helianthus Annuus (sunflower) Extract, Behenic Acid, Cetyl Behenate, Isostearyl Isostearate, Trisodium Ethylenediamine Disuccinate, Tocopherol, Allantoin, Rosmarinus Officinialis (Rosemary) Leaf Extract, Caprylic/Capric Triglyceride, Panthenol, Pentasodium Triphosphate, Citric Acid

PACKAGE LABEL

Everyday Sunscreen with Sunflower Extract

Broad Spectrum SPF 30

2.4 fl. oz. 71 ml

Everyday Sunscreen with Sunflower Extract

Broad Spectrum SPF 30

162 ml